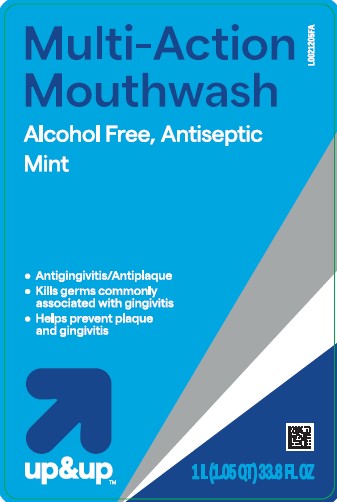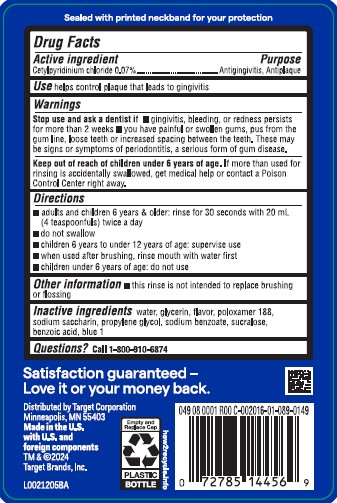 DRUG LABEL: Antiseptic
NDC: 11673-299 | Form: MOUTHWASH
Manufacturer: Target Corporation
Category: otc | Type: HUMAN OTC DRUG LABEL
Date: 20260218

ACTIVE INGREDIENTS: CETYLPYRIDINIUM CHLORIDE 0.7 mg/1 mL
INACTIVE INGREDIENTS: WATER; GLYCERIN; POLOXAMER 188; SACCHARIN SODIUM; PROPYLENE GLYCOL; SODIUM BENZOATE; SUCRALOSE; BENZOIC ACID; FD&C BLUE NO. 1

Up & Up 299.005/299AK-AL
Multi Action Alcohol Free Antiseptic Rinse w/CPC

Tamper Evident Statement

Sealed with printed neckband for your protection

Active ingredient

Cetylpyridinium chloride 0.07%

Purpose

Antigingivitis, Antiplaque

Use

helps control plaque that leads to gingivitis

Warnings

for this product

Stop use and ask a dentist if

- gingivitis, bleeding, or redness persists for more than 2 weeks
- you have painful or swollen gums, pus from the gum line, loose teeth or increased spacing between the teeth. These may be signs or symptoms of periodontitis, a serious form of gum disease.

Keep out of reach of children under 6 years of age.

If more than used for rinsing is accidentally swallowed, get medical help or contact a Poison Control Center right away.

Directions

- adults and children 6 years & older: rinse for 30 seconds with 20 mL (4 teaspoonfuls) twice a day
- do not swallow
- children 6 years to under 12 years of age: supervise use
- when used after brushing, rinse mouth with water first
- children under 6 years of age: do not use

Other information

- this rinse is not intended to replace brushing or flossing

Inactive ingredients

water, glycerin, flavor, poloxamer 188, sodium saccharin, propylene glycol, sodium benzoate, sucralose, benzoic acid, blue 1

Questions?

Call 1-800-910-6874

Adverse Reaction

Satisfaction guaranteed - Love it or your money back.

Distributed by Target Corporation

Minneapolis, MN 55403

Made in U.S. with U.S. and foreign components

TM & ©2024

Target Brands, Inc.

Empty and Replace Cap

PLASTIC BOTTLE

how2recycle.info

Principal display panel

Multi-Action Mouthwash

Alcohol Free, Antiseptic

Mint

- Antigingivitis/Antiplaque
- Kills germs commonly associated with gingivitis
- Helps prevent plaque and gingivitis

up&up™

1 L (1.05 QT) 33.8 FL OZ